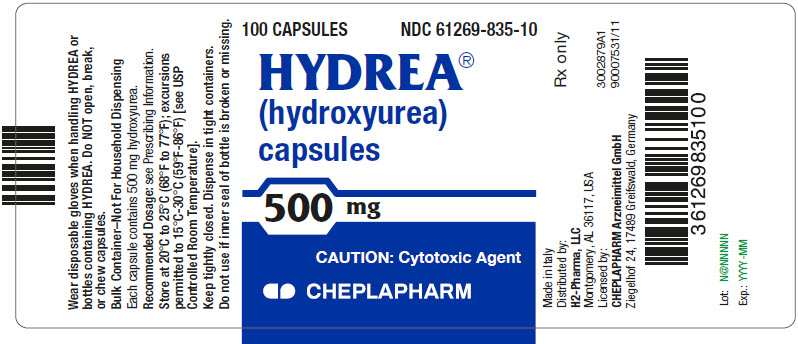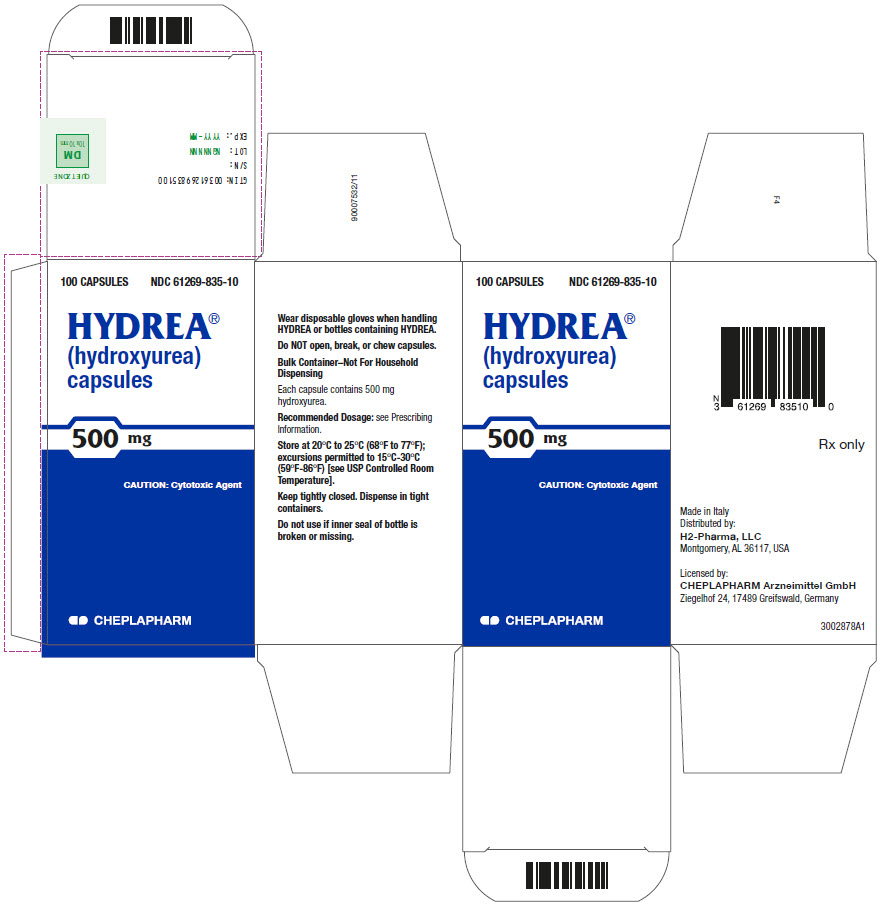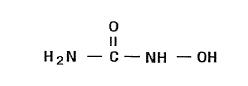 DRUG LABEL: HYDREA
NDC: 61269-835 | Form: CAPSULE
Manufacturer: H2-Pharma LLC
Category: prescription | Type: HUMAN PRESCRIPTION DRUG LABEL
Date: 20260126

ACTIVE INGREDIENTS: hydroxyurea 500 mg/1 1
INACTIVE INGREDIENTS: citric acid monohydrate; D&C Yellow No. 10; FD&C Blue No. 1; FD&C Red No. 40; D&C Red No. 28; GELATIN, UNSPECIFIED; LACTOSE, UNSPECIFIED FORM; magnesium stearate; sodium phosphate; titanium dioxide

HIGHLIGHTS OF PRESCRIBING INFORMATION

These highlights do not include all the information needed to use HYDREA safely and effectively. See full prescribing information for HYDREA.
HYDREA (hydroxyurea) capsules, for oral use
Initial U.S. Approval: 1967

RECENT MAJOR CHANGES

Warnings and Precautions, Laboratory Test Interference (5.11) 11/2023

Drug Interactions, Laboratory Test Interference (7.2) 11/2023

1 INDICATIONS AND USAGE

HYDREA is an antimetabolite indicated for the treatment of:

- Resistant chronic myeloid leukemia. (1)

- Locally advanced squamous cell carcinomas of the head and neck, (excluding lip) in combination with concurrent chemoradiation. (1)

2 DOSAGE AND ADMINISTRATION

- Individualize treatment based on tumor type, disease state, response to treatment, patient risk factors, and current clinical practice standards. (2.1)
- Renal impairment: Reduce the dose of HYDREA by 50% in patients with creatinine clearance less than 60 mL/min. (2.3, 8.6, 12.3)

3 DOSAGE FORMS AND STRENGTHS

- Capsules: 500 mg (3)

4 CONTRAINDICATIONS

- In patients who have demonstrated a previous hypersensitivity to hydroxyurea or any other component of its formulation. (4)

5 WARNINGS AND PRECAUTIONS

- Myelosuppression: Do not give if bone marrow function is markedly depressed. Monitor blood counts at baseline and throughout treatment. Interrupt treatment and reduce dose as necessary. (5.1)
- Hemolytic anemia: Monitor blood counts throughout treatment. If hemolysis persists, discontinue HYDREA. (5.2)
- Malignancies: Advise protection from sun exposure and monitor for secondary malignancies. (5.3)
- Embryo-Fetal toxicity: Can cause fetal harm. Advise of potential risk to a fetus and use of effective contraception. (5.4, 8.1, 8.3)
- Vasculitic toxicities: Discontinue HYDREA and initiate treatment if this occurs. (5.5)
- Live Vaccinations: Avoid live vaccine use in a patient taking HYDREA. (5.6)
- Risks with concomitant use of antiretroviral drugs: Pancreatitis, hepatotoxicity, and neuropathy have occurred. Monitor for signs and symptoms in patients with HIV infection using antiretroviral drugs; discontinue HYDREA and implement treatment. (5.7)
- Radiation recall: Monitor for skin erythema in patients who previously received radiation and manage symptomatically. (5.8)

6 ADVERSE REACTIONS

Most common adverse reactions (≥30%) are hematological, gastrointestinal symptoms, and anorexia. (6)

To report SUSPECTED ADVERSE REACTIONS, contact CHEPLAPHARM Arzneimittel GmbH at 1-888-877-5884 or FDA at 1-800-FDA-1088 or www.fda.gov/medwatch.

7 DRUG INTERACTIONS

- Antiretroviral drugs (7.1)
- Laboratory Test Interference. (7.2)

8 USE IN SPECIFIC POPULATIONS

- Lactation: Advise women not to breastfeed. (8.2)
- Geriatric Use: Care should be taken in dose selection and may require a lower dose regimen and monitoring of renal function. (8.5)

FULL PRESCRIBING INFORMATION

RECENT MAJOR CHANGES

HYDREA is indicated for the treatment of:

- Resistant chronic myeloid leukemia
- Locally advanced squamous cell carcinomas of the head and neck (excluding the lip) in combination with chemoradiation.

1 INDICATIONS AND USAGE

HYDREA is indicated for the treatment of:

- Resistant chronic myeloid leukemia.
- Locally advanced squamous cell carcinomas of the head and neck (excluding the lip) in combination with chemoradiation.

2 DOSAGE AND ADMINISTRATION

2.1 Dosing Information

HYDREA is used alone or in conjunction with other antitumor agents or radiation therapy to treat neoplastic diseases. Individualize treatment based on tumor type, disease state, response to treatment, patient risk factors, and current clinical practice standards.

Base all dosage on the patient's actual or ideal weight, whichever is less.

HYDREA is a cytotoxic drug. Follow applicable special handling and disposal procedures [see References (15)].

Swallow HYDREA capsules whole. Do NOT open, break, or chew capsules because HYDREA is a cytotoxic drug.

Prophylactic administration of folic acid is recommended [see Warnings and Precautions (5.8)].

Monitor blood counts at least once a week during HYDREA therapy. Severe anemia must be corrected before initiating therapy with HYDREA.

2.2 Dose Modifications for Toxicity

Monitor for the following and reduce the dose or discontinue HYDREA accordingly:

- Myelosuppression [see Warnings and Precautions (5.1)]
- Cutaneous vasculitis [see Warnings and Precautions (5.5)]

Consider dose modifications for other toxicities.

2.3 Dose Modifications for Renal Impairment

Reduce the dose of HYDREA by 50% in patients with measured creatinine clearance of less than 60 mL/min or with end-stage renal disease (ESRD) [see Use in Specific Populations (8.6) and Clinical Pharmacology (12.3)].

Creatinine Clearance (mL/min) | Recommended HYDREA Initial Dose (mg/kg once daily)
≥60 | 15
<60 or ESRD* | 7.5

* On dialysis days, administer HYDREA to patients following hemodialysis.

Close monitoring of hematologic parameters is advised in these patients.

3 DOSAGE FORMS AND STRENGTHS

Capsules: 500 mg opaque green cap and opaque pink body imprinted with "HYDREA" and "500".

4 CONTRAINDICATIONS

HYDREA is contraindicated in patients who have demonstrated a previous hypersensitivity to hydroxyurea or any other component of the formulation.

5 WARNINGS AND PRECAUTIONS

5.1 Myelosuppression

Hydroxyurea causes severe myelosuppression. Treatment with HYDREA should not be initiated if bone marrow function is markedly depressed. Bone marrow suppression may occur, and leukopenia is generally its first and most common manifestation. Thrombocytopenia and anemia occur less often and are seldom seen without a preceding leukopenia. Bone marrow depression is more likely in patients who have previously received radiotherapy or cytotoxic cancer chemotherapeutic agents; use HYDREA cautiously in such patients.

Evaluate hematologic status prior to and during treatment with HYDREA. Provide supportive care and modify dose or discontinue HYDREA as needed. Recovery from myelosuppression is usually rapid when therapy is interrupted.

5.2 Hemolytic Anemia

Cases of hemolytic anemia in patients treated with HYDREA for myeloproliferative diseases have been reported [see Adverse Reactions (6.1)]. Patients who develop acute jaundice or hematuria in the presence of persistent or worsening of anemia should have laboratory tests evaluated for hemolysis (e.g., measurement of serum lactate dehydrogenase, haptoglobin, reticulocyte, unconjugated bilirubin levels, urinalysis, and direct and indirect antiglobulin [Coombs] tests). In the setting of confirmed diagnosis of hemolytic anemia and in the absence of other causes, discontinue HYDREA.

5.3 Malignancies

Hydroxyurea is a human carcinogen. In patients receiving long-term hydroxyurea for myeloproliferative disorders, secondary leukemia has been reported. Skin cancer has also been reported in patients receiving long-term hydroxyurea. Advise protection from sun exposure and monitor for the development of secondary malignancies.

5.4 Embryo-Fetal Toxicity

Based on the mechanism of action and findings in animals, HYDREA can cause fetal harm when administered to a pregnant woman. Hydroxyurea was embryotoxic and teratogenic in rats and rabbits at doses 0.8 times and 0.3 times, respectively, the maximum recommended human daily dose on a mg/m^2 basis. Advise pregnant women of the potential risk to a fetus [see Use in Specific Populations (8.1)].
Advise females of reproductive potential to use effective contraception during and after treatment with HYDREA for at least 6 months after therapy. Advise males of reproductive potential to use effective contraception during and after treatment with HYDREA for at least 1 year after therapy [see Use in Specific Populations (8.1, 8.3)].

5.5 Vasculitic Toxicities

Cutaneous vasculitic toxicities, including vasculitic ulcerations and gangrene, have occurred in patients with myeloproliferative disorders during therapy with hydroxyurea. These vasculitic toxicities were reported most often in patients with a history of, or currently receiving, interferon therapy. If cutaneous vasculitic ulcers occur, institute treatment and discontinue HYDREA.

5.6 Live Vaccinations

Avoid use of live vaccine in patients taking HYDREA. Concomitant use of HYDREA with a live virus vaccine may potentiate the replication of the virus and/or may increase the adverse reaction of the vaccine because normal defense mechanisms may be suppressed by HYDREA. Vaccination with live vaccines in a patient receiving HYDREA may result in severe infection. Patient's antibody response to vaccines may be decreased. Consider consultation with a specialist.

5.7 Risks with Concomitant Use of Antiretroviral Drugs

Pancreatitis, hepatotoxicity, and peripheral neuropathy have occurred when hydroxyurea was administered concomitantly with antiretroviral drugs, including didanosine and stavudine [see Drug Interactions (7.1)].

5.8 Radiation Recall

Patients who have received irradiation therapy in the past may have an exacerbation of post-irradiation erythema. Monitor for skin erythema in patients who previously received radiation and manage symptomatically.

5.9 Macrocytosis

HYDREA may cause macrocytosis, which is self-limiting, and is often seen early in the course of treatment. The morphologic change resembles pernicious anemia, but is not related to vitamin B12 or folic acid deficiency. This may mask the diagnosis of pernicious anemia. Prophylactic administration of folic acid is recommended.

5.10 Pulmonary Toxicity

Interstitial lung disease including pulmonary fibrosis, lung infiltration, pneumonitis, and alveolitis/allergic alveolitis (including fatal cases) have been reported in patients treated for myeloproliferative neoplasm. Monitor patients developing pyrexia, cough, dyspnea, or other respiratory symptoms frequently, investigate and treat promptly. Discontinue HYDREA and manage with corticosteroids [see Adverse Reactions (6.1)].

5.11 Laboratory Test Interference

Interference with Uric Acid, Urea, or Lactic Acid Assays is possible, rendering falsely elevated results of these in patients treated with hydroxyurea [see Drug Interactions (7.2)].

Hydroxyurea may falsely elevate sensor glucose results from certain continuous glucose monitoring (CGM) systems and may lead to hypoglycemia if sensor glucose results are relied upon to dose insulin.
If a patient using a CGM is to be prescribed hydroxyurea, consult with the CGM prescriber about alternative glucose monitoring methods [see Drug Interactions (7.2)].

6 ADVERSE REACTIONS

The following clinically significant adverse reactions are described in detail in other labeling sections:

- Myelosuppression [see Warnings and Precautions (5.1)]
- Hemolytic anemia [see Warnings and Precautions (5.2)]
- Malignancies [see Warnings and Precautions (5.3)]
- Vasculitic toxicities [see Warnings and Precautions (5.5)]
- Risks with concomitant use of antiretroviral drugs [see Warnings and Precautions (5.7)]
- Radiation recall [see Warnings and Precautions (5.8)]
- Macrocytosis [see Warnings and Precautions (5.9)]
- Pulmonary Toxicity [see Warnings and Precautions (5.10)]

6.1 Postmarketing Experience

The following adverse reactions have been identified during post-approval use of HYDREA. Because these reactions are reported voluntarily from a population of uncertain size, it is not always possible to reliably estimate their frequency.

- Reproductive System and Breast disorders: azoospermia, and oligospermia
- Gastrointestinal disorders: stomatitis, nausea, vomiting, diarrhea, and constipation
- Metabolism and Nutrition disorders: anorexia, tumor lysis syndrome
- Skin and subcutaneous tissue disorders: maculopapular rash, skin ulceration, cutaneous lupus erythematosus, dermatomyositis-like skin changes, peripheral and facial erythema, hyperpigmentation, nail hyperpigmentation, atrophy of skin and nails, scaling, violet papules, and alopecia
- Renal and urinary disorders: dysuria, elevations in serum uric acid, blood urea nitrogen (BUN), and creatinine levels
- Nervous system disorders: headache, dizziness, drowsiness, disorientation, hallucinations, and convulsions
- General Disorders: fever, chills, malaise, edema, and asthenia
- Hepatobiliary disorders: elevation of hepatic enzymes, cholestasis, and hepatitis
- Respiratory disorders: diffuse pulmonary infiltrates, dyspnea, and pulmonary fibrosis, interstitial lung disease, pneumonitis, alveolitis, allergic alveolitis and cough
- Immune disorders: systemic lupus erythematosus
- Hypersensitivity: Drug-induced fever (pyrexia) (>39°C, >102°F) requiring hospitalization has been reported concurrently with gastrointestinal, pulmonary, musculoskeletal, hepatobiliary, dermatological or cardiovascular manifestations. Onset typically occurred within 6 weeks of initiation and resolved upon discontinuation of hydroxyurea. Upon re-administration fever re-occurred typically within 24 hours.
- Blood and lymphatic system disorders: hemolytic anemia

Adverse reactions observed with combined hydroxyurea and irradiation therapy are similar to those reported with the use of hydroxyurea or radiation treatment alone. These effects primarily include bone marrow depression (anemia and leukopenia), gastric irritation, and mucositis. Almost all patients receiving an adequate course of combined hydroxyurea and irradiation therapy will demonstrate concurrent leukopenia. Platelet depression (<100,000 cells/mm^3) has occurred in the presence of marked leukopenia. HYDREA may potentiate some adverse reactions usually seen with irradiation alone, such as gastric distress and mucositis.

7 DRUG INTERACTIONS

7.1 Increased Toxicity with Concomitant Use of Antiretroviral Drugs

Pancreatitis

In patients with HIV infection during therapy with hydroxyurea and didanosine, with or without stavudine, fatal and nonfatal pancreatitis have occurred. Hydroxyurea is not indicated for the treatment of HIV infection; however, if patients with HIV infection are treated with hydroxyurea, and in particular, in combination with didanosine and/or stavudine, close monitoring for signs and symptoms of pancreatitis is recommended. Permanently discontinue therapy with HYDREA in patients who develop signs and symptoms of pancreatitis.

Hepatotoxicity

Hepatotoxicity and hepatic failure resulting in death have been reported during postmarketing surveillance in patients with HIV infection treated with hydroxyurea and other antiretroviral drugs. Fatal hepatic events were reported most often in patients treated with the combination of hydroxyurea, didanosine, and stavudine. Avoid this combination.

Peripheral Neuropathy

Peripheral neuropathy, which was severe in some cases, has been reported in patients with HIV infection receiving hydroxyurea in combination with antiretroviral drugs, including didanosine, with or without stavudine.

7.2 Laboratory Test Interference

Interference with Uric Acid, Urea, or Lactic Acid Assays

Studies have shown that there is an analytical interference of hydroxyurea with the enzymes (urease, uricase, and lactate dehydrogenase) used in the determination of urea, uric acid, and lactic acid, rendering falsely elevated results of these in patients treated with hydroxyurea.

Interference with Continuous Glucose Monitoring Systems

Hydroxyurea may falsely elevate sensor glucose results from certain continuous glucose monitoring (CGM) systems and may lead to hypoglycemia if sensor glucose results are relied upon to dose insulin.
If a patient using CGM is to be prescribed hydroxyurea, consult with the CGM prescriber about alternative glucose monitoring methods.

8 USE IN SPECIFIC POPULATIONS

8.1 Pregnancy

Risk Summary

HYDREA can cause fetal harm based on findings from animal studies and the drug's mechanism of action [see Clinical Pharmacology (12.1)]. There are no data with HYDREA use in pregnant women to inform a drug-associated risk. In animal reproduction studies, administration of hydroxyurea to pregnant rats and rabbits during organogenesis produced embryotoxic and teratogenic effects at doses 0.8 times and 0.3 times, respectively, the maximum recommended human daily dose on a mg/m^2 basis (see Data). Advise women of the potential risk to a fetus and to avoid becoming pregnant while being treated with HYDREA.

In the U.S. general population, the estimated background risk of major birth defects and miscarriage in clinically recognized pregnancies is 2%–4% and 15%–20%, respectively.

Data

Animal Data

Hydroxyurea has been demonstrated to be a potent teratogen in a wide variety of animal models, including mice, hamsters, cats, miniature swine, dogs, and monkeys at doses within 1-fold of the human dose given on a mg/m^2 basis. Hydroxyurea is embryotoxic and causes fetal malformations (partially ossified cranial bones, absence of eye sockets, hydrocephaly, bipartite sternebrae, missing lumbar vertebrae) at 180 mg/kg/day (about 0.8 times the maximum recommended human daily dose on a mg/m^2 basis) in rats and at 30 mg/kg/day (about 0.3 times the maximum recommended human daily dose on a mg/m^2 basis) in rabbits. Embryotoxicity was characterized by decreased fetal viability, reduced live litter sizes, and developmental delays. Hydroxyurea crosses the placenta. Single doses of ≥375 mg/kg (about 1.7 times the maximum recommended human daily dose on a mg/m^2 basis) to rats caused growth retardation and impaired learning ability.

8.2 Lactation

Risk Summary

Hydroxyurea is excreted in human milk. Because of the potential for serious adverse reactions in a breastfed infant from hydroxyurea, including carcinogenicity, discontinue breastfeeding during treatment with HYDREA.

8.3 Females and Males of Reproductive Potential

Pregnancy Testing

Verify the pregnancy status of females of reproductive potential prior to initiating HYDREA therapy.

Contraception

Females

HYDREA can cause fetal harm when administered to a pregnant woman [see Use in Specific Populations (8.1)]. Advise females of reproductive potential to use effective contraception during and after treatment with HYDREA for at least 6 months after therapy. Advise females to immediately report pregnancy.

Males

HYDREA may damage spermatozoa and testicular tissue, resulting in possible genetic abnormalities. Males with female sexual partners of reproductive potential should use effective contraception during and after treatment with HYDREA for at least 1 year after therapy [see Nonclinical Toxicology (13.1)].

Infertility

Males

Based on findings in animals and humans, male fertility may be compromised by treatment with HYDREA. Azoospermia or oligospermia, sometimes reversible, has been observed in men. Inform male patients about the possibility of sperm conservation before the start of therapy [see Adverse Reactions (6) and Nonclinical Toxicology (13.1)].

8.4 Pediatric Use

Safety and effectiveness in pediatric patients have not been established.

8.5 Geriatric Use

Elderly patients may be more sensitive to the effects of hydroxyurea and may require a lower dose regimen. Hydroxyurea is excreted by the kidney, and the risk of adverse reactions to this drug may be greater in patients with impaired renal function. Because elderly patients are more likely to have decreased renal function, care should be taken in dose selection, and it may be useful to monitor renal function [see Dosage and Administration (2.3)].

8.6 Renal Impairment

The exposure to hydroxyurea is higher in patients with creatinine clearance of less than 60 mL/min or in patients with end-stage renal disease (ESRD). Reduce dosage and closely monitor the hematologic parameters when HYDREA is to be administered to these patients [see Dosage and Administration (2.3) and Clinical Pharmacology (12.3)].

8.7 Hepatic Impairment

There are no data that support specific guidance for dosage adjustment in patients with hepatic impairment. Close monitoring of hematologic parameters is advised in these patients.

10 OVERDOSAGE

Acute mucocutaneous toxicity has been reported in patients receiving hydroxyurea at dosages several times the therapeutic dose. Soreness, violet erythema, edema on palms and soles followed by scaling of hands and feet, severe generalized hyperpigmentation of the skin, and stomatitis have also been observed.

11 DESCRIPTION

HYDREA (hydroxyurea capsules, USP) is an antimetabolite available for oral use as capsules containing 500 mg hydroxyurea. Inactive ingredients include citric acid, colorants (D&C Yellow No. 10, FD&C Blue No. 1, FD&C Red No. 40, and D&C Red No. 28), gelatin, lactose, magnesium stearate, sodium phosphate, and titanium dioxide.

Hydroxyurea is a white to off-white crystalline powder. It is hygroscopic and freely soluble in water, but practically insoluble in alcohol. The empirical formula is CH4N2O2 and it has a molecular weight of 76.05. Its structural formula is:

12 CLINICAL PHARMACOLOGY

12.1 Mechanism of Action

The precise mechanism by which hydroxyurea produces its antineoplastic effects cannot, at present, be described. However, the reports of various studies in tissue culture in rats and humans lend support to the hypothesis that hydroxyurea causes an immediate inhibition of DNA synthesis by acting as a ribonucleotide reductase inhibitor, without interfering with the synthesis of ribonucleic acid or of protein. This hypothesis explains why, under certain conditions, hydroxyurea may induce teratogenic effects.

Three mechanisms of action have been postulated for the increased effectiveness of concomitant use of hydroxyurea therapy with irradiation on squamous cell (epidermoid) carcinomas of the head and neck. In vitro studies utilizing Chinese hamster cells suggest that hydroxyurea (1) is lethal to normally radioresistant S-stage cells, and (2) holds other cells of the cell cycle in the G1 or pre-DNA synthesis stage where they are most susceptible to the effects of irradiation. The third mechanism of action has been theorized on the basis of in vitro studies of HeLa cells. It appears that hydroxyurea, by inhibition of DNA synthesis, hinders the normal repair process of cells damaged but not killed by irradiation, thereby decreasing their survival rate; RNA and protein syntheses have shown no alteration.

12.3 Pharmacokinetics

Absorption

Following oral administration of HYDREA, hydroxyurea reaches peak plasma concentrations in 1 to 4 hours. Mean peak plasma concentrations and AUCs increase more than proportionally with increase of dose.

There are no data on the effect of food on the absorption of hydroxyurea.

Distribution

Hydroxyurea distributes throughout the body with a volume of distribution approximating total body water.

Hydroxyurea concentrates in leukocytes and erythrocytes.

Metabolism

Up to 60% of an oral dose undergoes conversion through saturable hepatic metabolism and a minor pathway of degradation by urease found in intestinal bacteria.

Excretion

In patients with sickle cell anemia, the mean cumulative urinary recovery of hydroxyurea was about 40% of the administered dose.

Specific Populations

Renal Impairment

The effect of renal impairment on the pharmacokinetics of hydroxyurea was assessed in adult patients with sickle cell disease and renal impairment. Patients with normal renal function (creatinine clearance [CrCl] >80 mL/min), mild (CrCl 50‑80 mL/min), moderate (CrCl = 30-<50 mL/min), or severe (<30 mL/min) renal impairment received a single oral dose of 15 mg/kg hydroxyurea. Patients with ESRD received two doses of 15 mg/kg separated by 7 days; the first was given following a 4-hour hemodialysis session, the second prior to hemodialysis. The exposure to hydroxyurea (mean AUC) in patients with CrCl <60 mL/min and those with ESRD was 64% higher than in patients with normal renal function (CrCl >60 mL/min). Reduce the dose of HYDREA when it is administered to patients with creatinine clearance of <60 mL/min or with ESRD following hemodialysis [see Dosage and Administration (2.3) and Use in Specific Populations (8.6)].

13 NONCLINICAL TOXICOLOGY

13.1 Carcinogenesis, Mutagenesis, Impairment of Fertility

Conventional long-term studies to evaluate the carcinogenic potential of hydroxyurea have not been performed. However, intraperitoneal administration of 125 to 250 mg/kg hydroxyurea (about 0.6-1.2 times the maximum recommended human oral daily dose on a mg/m^2 basis) thrice weekly for 6 months to female rats increased the incidence of mammary tumors in rats surviving to 18 months compared to control. Hydroxyurea is mutagenic in vitro to bacteria, fungi, protozoa, and mammalian cells. Hydroxyurea is clastogenic in vitro (hamster cells, human lymphoblasts) and in vivo (SCE assay in rodents, mouse micronucleus assay). Hydroxyurea causes the transformation of rodent embryo cells to a tumorigenic phenotype.

Hydroxyurea administered to male rats at 60 mg/kg/day (about 0.3 times the maximum recommended human daily dose on a mg/m^2 basis) produced testicular atrophy, decreased spermatogenesis, and significantly reduced their ability to impregnate females.

15 REFERENCES

OSHA. http://www.osha.gov/SLTC/hazardousdrugs/index.html.

16 HOW SUPPLIED/STORAGE AND HANDLING

16.1 How Supplied

HYDREA® (hydroxyurea capsules, USP) is supplied as 500 mg capsules in HDPE bottles with a plastic safety screw cap. Each bottle contains 100 capsules. The cap is opaque green and the body is opaque pink. The capsules are imprinted on both sections with "HYDREA" and "500" in black ink (NDC 61269-835-10).

16.2 Storage

Store at 20°C-25°C (68°F -77°F); excursions permitted to 15°C-30°C (59°F-86°F) [see USP Controlled Room Temperature]. Keep tightly closed.

16.3 Handling and Disposal

HYDREA is a cytotoxic drug. Follow applicable special handling and disposal procedures [see References (15)].

To decrease the risk of contact, advise caregivers to wear disposable gloves when handling HYDREA or bottles containing HYDREA. Wash hands with soap and water before and after contact with the bottle or capsules when handling HYDREA. Do not open HYDREA capsules. Avoid exposure to crushed or opened capsules. If contact with crushed or opened capsules occurs on the skin, wash affected area immediately and thoroughly with soap and water. If contact with crushed or opened capsules occurs on the eye(s), the affected area should be flushed thoroughly with water or isotonic eyewash designated for that purpose for at least 15 minutes. If the powder from the capsule is spilled, immediately wipe it up with a damp disposable towel and discard in a closed container, such as a plastic bag; as should the empty capsules. The spill areas should then be cleaned three times using a detergent solution followed by clean water. Keep the medication away from children and pets. Contact your doctor for instructions on how to dispose of outdated capsules.

17 PATIENT COUNSELING INFORMATION

- There is a risk of myelosuppression. Monitoring blood counts weekly throughout the duration of therapy should be emphasized to patients taking HYDREA. Advise patients to report signs and symptoms of infection or bleeding immediately [see Warnings and Precautions (5.1)].
- Advise patients of the risk of hemolytic anemia. Advise patients that they will have blood tests to evaluate for this if they develop persistent anemia [see Warnings and Precautions (5.2)].
- Advise patients that there is a risk of cutaneous vasculitic toxicities and secondary malignancies including leukemia and skin cancers [see Warnings and Precautions (5.3, 5.5)].
- Advise females of reproductive potential of the potential risk to a fetus and to inform their healthcare provider of a known or suspected pregnancy. Advise females and males of reproductive potential to use contraception during and after treatment with HYDREA [see Warnings and Precautions (5.4) and Use in Specific Populations (8.1, 8.3)].
- Advise patients to inform their healthcare provider if they have received or are planning to receive vaccinations while taking HYDREA as this may result in a severe infection [see Warnings and Precautions (5.6)].
- Advise females to discontinue breastfeeding during treatment with HYDREA [see Use in Specific Populations (8.2)].
- Patients with HIV infection should contact their physician for signs and symptoms of pancreatitis, hepatic events, and peripheral neuropathy [see Warnings and Precautions (5.7)].
- Post-irradiation erythema can occur in patients who have received previous irradiation therapy [see Warnings and Precautions (5.8)].
- Advise patients of the symptoms of potential pulmonary toxicity and instruct them to seek prompt medical attention in the event of pyrexia, cough, dyspnea, or other respiratory symptoms [see Warnings and Precautions (5.10)].
- Advise patients to notify their healthcare provider if they are using a continuous glucose monitoring system while taking HYDREA [see Warnings and Precautions (5.11)].

PRINCIPAL DISPLAY PANEL - 500 mg Capsule Bottle Label

100 CAPSULES
NDC 61269-835-10

HYDREA®
(hydroxyurea)
capsules

500 mg

CAUTION: Cytotoxic Agent

CHEPLAPHARM

PRINCIPAL DISPLAY PANEL - 500 mg Capsule Bottle Carton

100 CAPSULES
NDC 61269-835-10

HYDREA®
(hydroxyurea)
capsules

500 mg

CAUTION: Cytotoxic Agent

CHEPLAPHARM